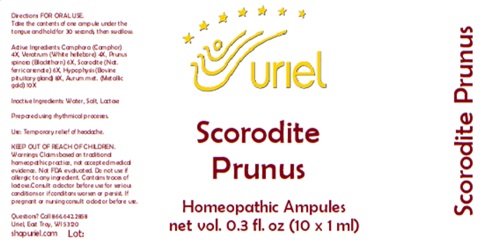 DRUG LABEL: Scorodite Prunus
NDC: 48951-8168 | Form: LIQUID
Manufacturer: Uriel Pharmacy Inc.
Category: homeopathic | Type: HUMAN OTC DRUG LABEL
Date: 20250120

ACTIVE INGREDIENTS: CAMPHOR (NATURAL) 4 [hp_X]/1 mL; VERATRUM ALBUM ROOT 4 [hp_X]/1 mL; SLOE 6 [hp_X]/1 mL; FERROUS ARSENATE 6 [hp_X]/1 mL; BOS TAURUS PITUITARY GLAND 8 [hp_X]/1 mL; GOLD 10 [hp_X]/1 mL
INACTIVE INGREDIENTS: WATER; SODIUM CHLORIDE; LACTOSE

Scorodite Prunus

INDICATIONS AND USAGE

Directions: FOR ORAL USE ONLY.

DOSAGE AND ADMINISTRATION

Take the contents of one ampule under the tongue and hold for 30 seconds, then swallow.

ACTIVE INGREDIENT

Active Ingredients: Camphora (Camphor) 4X, Veratrum (White hellebore) 4X, Prunus spinosa (Blackthorn) 6X, Scorodite (Nat. ferric arsenate) 6X, Hypophysis (Bovine pituitary gland) 8X, Aurum met. (Metallic gold) 10X

Inactive Ingredients: Water, Salt, Lactose

Prepared using rhythmical processes.

PURPOSE

Use: Temporary relief of headache.

KEEP OUT OF REACH OF CHILDREN.

WARNINGS

Warnings: Claims based on traditional homeopathic practice, not accepted medical evidence. Not FDA evaluated. Do not use if allergic to any ingredient. Contains traces of lactose. Consult a doctor before use for serious conditions or if conditons worsen or persist. If pregnant or nursing consult a doctor before use.

Questions? Call 866.642.2858
Uriel, East Troy, WI 53120
shopuriel.com Lot: